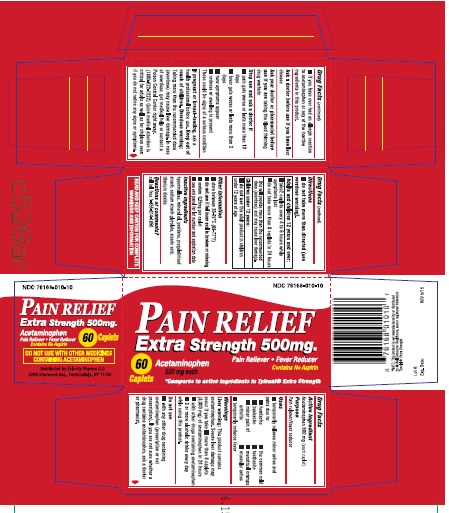 DRUG LABEL: Acetaminophen
NDC: 76168-120 | Form: TABLET
Manufacturer: Velocity Pharma LLC
Category: otc | Type: HUMAN OTC DRUG LABEL
Date: 20180514

ACTIVE INGREDIENTS: ACETAMINOPHEN 500 mg/1 1
INACTIVE INGREDIENTS: STARCH, CORN; POVIDONE K30; SODIUM METABISULFITE; SILICON DIOXIDE; HYPROMELLOSE 2910 (15 MPA.S); CELLULOSE, MICROCRYSTALLINE; CROSCARMELLOSE SODIUM; STEARIC ACID; SODIUM STARCH GLYCOLATE TYPE A POTATO; HYPROMELLOSE 2910 (6 MPA.S); POLYETHYLENE GLYCOL 1000; TITANIUM DIOXIDE

Acetaminophen Extra Strength 500 mg

Active Ingredient

(in each tablet)

Acetaminophen 500mg

Purpose

pain reliever/fever reducer

Uses

- temporarily reduces fever

Warnings

Liver Warning: This product contains acetaminophen. Severe liver damage may occur if you take

- more than 4000 mg of acetaminophen in 24 hours
- with other drugs containing acetaminophen
- 3 or more alcoholic drinks everyday while using this product

do not use

- with any other drug containing acetaminophen (prescription or not prescription). If you are not sure whether a drug contains acetaminophen, ask a doctor or pharmacist.
- If you have ever had an allergic reaction to acetaminophen or any of the inactive ingredients in this product.

ask a doctor before use if you have liver disease

ask your doctor or pharmacist before use if you are taking the blood thinning drug warfarin

Stop use and ask a doctor if:

- pain gets worse or lasts more than 10 days
- fever gets worse or lasts more than 3 days
- redness or swelling is present
- new symptoms appear

- these could be signs of a serious condition

If pregnant or breast-feeding, ask a health professional before use.

Keep out of reach of children.

Overdose warning: Taking more than recommended dose (overdose) may cause liver damage. In case of overdose, get medical help or contact a Poison Control Center right away. (1-800-222-1222) Quick medical attention is critical for adults as well as for children even if you do not notice any signs or symptoms.

Directions

- do not take more than directed (see overdose warning).
- Adults and children 12 years and over:
- take 2 caplets every 6 hours while symptoms last.
- do not take more than 6 caplets of this product in 24 hours, unless directed by a doctor
- do not take for more than 10 days unless directed by a doctor
  children under 12 years:
- Ask a doctor

Other Information

- Store at a controlled temperature between 62° and 77 °F)

Inactive Ingredients

P.G Starch, P.V.P.K.30, sodium metabisulfite, colloidal silicon dioxide, Hypromellose-15, Microcrystalline Cellulose, Croscarmellose Sodium, Stearic Acid, Sodium Starch Glycolate, Hypromellose-6, Polyethylene Glycol, Titanium Dioxide.

Questions or Comments

Questions? 1-855-314-1850